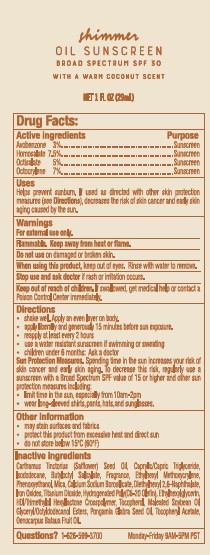 DRUG LABEL: TRADER JOES SHIMMER SUNSCREEN
NDC: 71270-160 | Form: OIL
Manufacturer: Trader Joe's Company
Category: otc | Type: HUMAN OTC DRUG LABEL
Date: 20250326

ACTIVE INGREDIENTS: OCTISALATE 5 g/100 mL; OCTOCRYLENE 7 g/100 mL; AVOBENZONE 3 g/100 mL; HOMOSALATE 7.5 g/100 mL
INACTIVE INGREDIENTS: SAFFLOWER OIL; MEDIUM-CHAIN TRIGLYCERIDES; ISODODECANE; BUTYLOCTYL SALICYLATE; ETHYLHEXYL METHOXYCRYLENE; MICA; CALCIUM SODIUM BOROSILICATE; DIETHYLHEXYL 2,6-NAPHTHALATE; ETHYLHEXYLGLYCERIN; FERRIC OXIDE RED; TITANIUM DIOXIDE; HYDROGENATED POLY(C6-20 OLEFIN); HDI/TRIMETHYLOL HEXYLLACTONE CROSSPOLYMER; TOCOPHEROL; SOYBEAN OIL; PHENOXYETHANOL; PONGAMIA GLABRA SEED OIL; OENOCARPUS BATAUA FRUIT OIL; .ALPHA.-TOCOPHEROL ACETATE

TRADER JOE’S (as PLD) - Shimmer Oil Sunscreen Broad Spectrum SPF 30 (71270-160)

ACTIVE INGREDIENTS

AVOBENZONE 3%

HOMOSALATE 7.5%

OCTISALATE 5%

OCTOCRYLENE 7%

PURPOSE

Sunscreen

USES

Helps prevent sunburn. If used as directed with other skin protection measures (See Directions), decreases the risk of skin cancer and early skin aging caused by the sun.

WARNINGS

For external use only.

Flammable. Keep away from heat or flame.

Do not use on damaged or broken skin.

When using this product,keep out of eyes. Rinse with water to remove.

Stop use and ask a doctor if rash or irritation occurs.

Keep out of reach of children. If swallowed, get medical help or contact a Poison Control Center immediately.

DIRECTIONS

- Shake well. Apply an even layer on body.
- Apply liberally and generously 15 minutes before sun exposure.
- Reapply at least every 2 hours.
- Use a water resistant sunscreen if swimming or sweating.
- Children under six months of age: Ask a doctor

Sun Protection Measures. Spending time in the sun increases your risk of skin cancer and early skin aging. To decrease this risk, regularly use a sunscreen with a Broad Spectrum SPF 15 value or higher along with other sun protection measures including:

- limit time in the sun, especially from 10 a.m. – 2 p.m.
- wear long-sleeved shirts, pants, hats and sunglasses.

INACTIVE INGREDIENTS

Carthamus Tinctorius (Safflower) Seed Oil, Caprylic/Capric Triglyceride, lsododecane, Butyloctyl Silicylate, Fragrance, Ethylhexyl Methoxycrylene, Phenoxyethanol, Mica, Calcium Sodum Borosilicate, Diethylhexyl 2,6-Naphthalate, Iron Oxides, Ttanium Dioxide, Hydrogenated Poly(C6-20 Olefin), Ethylhexylglycerin, HDI/Trimethylol Hexyllactone Crosspolymer, Tocopherol, Maleated Soybean OiI Glyceryl/Octyldodecanol Esters, Pongamia Glabra Seed Oil, Tocopheryl Acetate, Oenocarpus Bataua Fruit Oil.

QUESTIONS?

1- 626-599-3700

Monday – Friday 9 AM – 5 PM PST